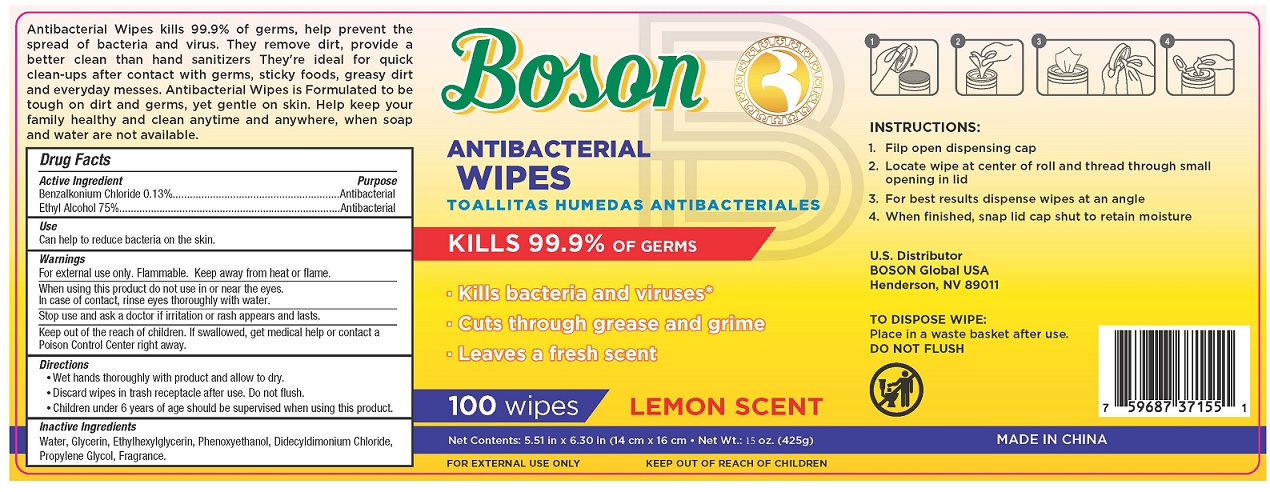 DRUG LABEL: Boson
NDC: 53325-126 | Form: CLOTH
Manufacturer: Almil Nutritional Products, Inc.
Category: otc | Type: HUMAN OTC DRUG LABEL
Date: 20200730

ACTIVE INGREDIENTS: ALCOHOL 0.75 mL/1 mL; BENZALKONIUM CHLORIDE 1.3 mg/1 mL
INACTIVE INGREDIENTS: WATER; GLYCERIN; ETHYLHEXYLGLYCERIN; PHENOXYETHANOL; DIDECYLDIMONIUM CHLORIDE; PROPYLENE GLYCOL; FRAGRANCE LEMON ORC2001060

Active Ingredient

Benzalkonium Chloride 0.13%

Ethyl Alcohol 75%

Purpose

Antibacterial

Uses

• to decrease bacteria on the skin that could cause disease
• recommended for repeated use

Warnings

For external use only - hands

Flammable, keep away from heat and flame

When using the product

- keep out of eyes, in case of contact with eyes, flush thoroughly with water
- avoid contact with broken skin

Keep out of reach of children. If swallowed, get medical help or contact a Poison Control Center right away.

Directions

- Wipe down surface thoroughly and allow to air-dry.
- Discard wipe in trash receptacle after use, do not flush.
- For children under 6, use only under adult supervision.
- Not recommended for infants.

Inactive ingredients

Purified water, glycerin, ethylhexyl glycerin, phenoxyethanol, didecyldimonium chloride, propylene glycol, fragrance